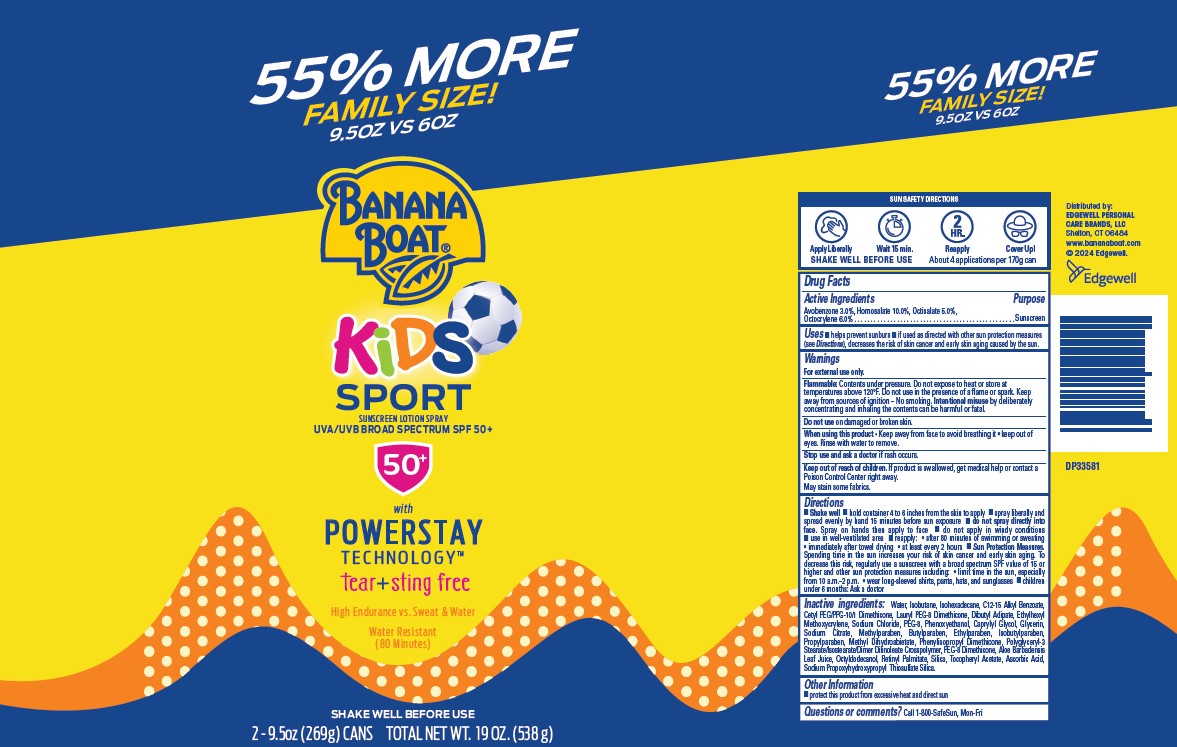 DRUG LABEL: Banana Boat
NDC: 63354-278 | Form: SPRAY
Manufacturer: Edgewell Personal Care Brands, LLC
Category: otc | Type: HUMAN OTC DRUG LABEL
Date: 20251106

ACTIVE INGREDIENTS: AVOBENZONE 3 g/100 g; HOMOSALATE 10 g/100 g; OCTISALATE 5 g/100 g; OCTOCRYLENE 6 g/100 g
INACTIVE INGREDIENTS: ALKYL (C12-15) BENZOATE; ISOHEXADECANE; CETYL PEG/PPG-10/1 DIMETHICONE (HLB 2); ALOE VERA LEAF; VITAMIN A PALMITATE; ASCORBIC ACID; SODIUM PROPOXYHYDROXYPROPYL THIOSULFATE SILICA; SODIUM CITRATE; METHYLPARABEN; ETHYLPARABEN; BUTYLPARABEN; ISOBUTYLPARABEN; METHYL DIHYDROABIETATE; PEG-8 DIMETHICONE; OCTYLDODECANOL; .ALPHA.-TOCOPHEROL ACETATE; WATER; ISOBUTANE; SODIUM CHLORIDE; POLYETHYLENE GLYCOL 400; CAPRYLYL GLYCOL; PROPYLPARABEN; SILICON DIOXIDE; DIBUTYL ADIPATE; ETHYLHEXYL METHOXYCRYLENE; PHENOXYETHANOL; GLYCERIN

Active Ingredients

Avobenzone 3%, Homosalate 10%, Octisalate 5%, Octocrylene 6%

Purpose

Sunscreen

Uses

• helps prevent sunburn • if used as directed with other sun protection measures (see Direction), decrease the risk of skin cancer and early skin aging caused by the sun.

Warnings

For external use only.

Flammable: Contents under pressure. Do not puncture or incinerate. Do not expose to heat or store at temperatures above 120°F. Do not use in the presence of a flame or spark. Keep away from sources of ignition – No smoking. Intentional misuse by deliberately concentrating and inhaling the contents can be harmful or fatal.

May stain some fabrics.

Do not use

on damaged or broken skin.

When using this product

• Keep away from face to avoid breathing it • keep out of eyes. Rinse with water to remove.

Stop use and ask a doctor

if rash occurs.

Keep out of reach of children

If product is swallowed, get medical help or contact a Poison Control Center right away.

Directions

• Shake well. • hold container 4 to 6 inches from the skin to apply • spray liberally and spread evenly by hand 15 minutes before sun exposure • do not spray directly into face. Spray on hands then apply to face • do not apply in windy conditions • use in well-ventilated area • reapply: • after 80 minutes of swimming or sweating • immediately after towel drying • at least every 2 hours • Sun Protection Measures. Spending time in the sun increases your risk of skin cancer and early skin aging. To decrease this risk, regularly use a sunscreen with a broad spectrum SPF value of 15 or higher and other sun protection measures including: • limit time in the sun, especially from 10 a.m.–2 p.m. • wear long-sleeved shirts, pants, hats, and sunglasses. Children under 6 months: Ask a doctor.

Inactive Ingredient

Water, Isobutane, Isohexadecane, C12-15 Alkyl Benzoate, Cetyl PEG/PPG-10/1 Dimethicone, Lauryl PEG-8 Dimethicone, Dibutyl Adipate, Ethylhexyl Methoxycrylene, Sodium Chloride, PEG-8, Phenoxyethanol, Caprylyl Glycol, Glycerin, Sodium Citrate, Methylparaben, Butylparaben, Ethylparaben, Isobutylparaben, Propylparaben, Methyl Dihydroabietate, Phenylisopropyl Dimethicone, Polyglyceryl-3 Stearate/Isostearate/Dimer Dilinoleate Crosspolymer, PEG-8 Dimethicone, Aloe Barbadensis Leaf Juice, Octyldodecanol, Retinyl Palmitate, Silica, Tocopheryl Acetate, Ascorbic Acid, Sodium Propoxyhydroxypropyl Thiosulfate Silica.

Other information

• protect this product from excessive heat and direct sun.

Questions or comments?

Call 1-800-SafeSun, Mon-Fri

PACKAGE LABEL

BANANA
BOAT®
TEAR +
STING FREE
PEDIATRICIAN
TESTED
LIGHTWEIGHT
QUICK
ABSORBING
HIGH
ENDURANCE
VS. SWEAT &
WATER
LASTS AS
LONG AS THE
FUN DOES
FREE FROM
Oxybenzone
Octinoxate
2 - 9.5 OZ. Kids Sport SPF 50+ Sunscreen Lotion Spray Total Net WT 19 OZ. (538 g)